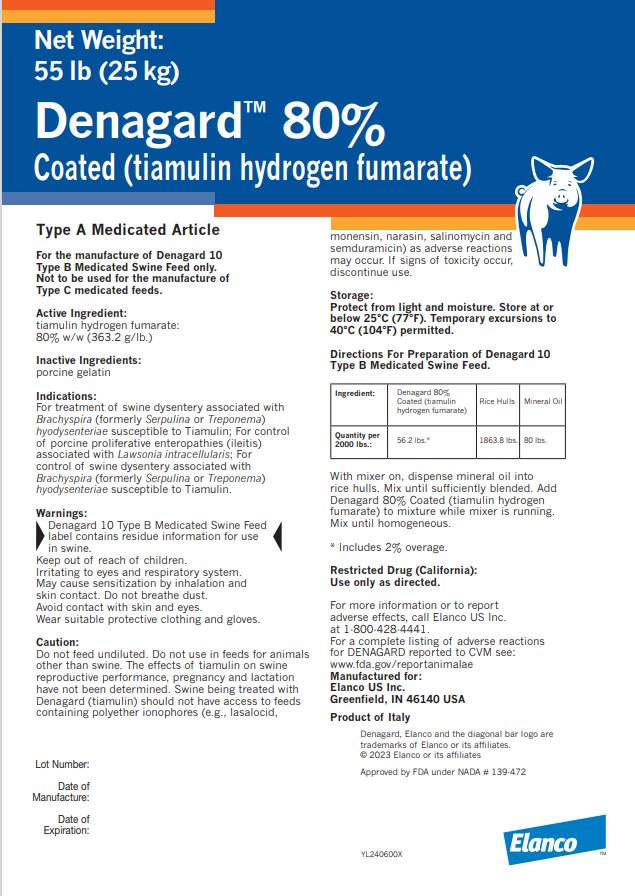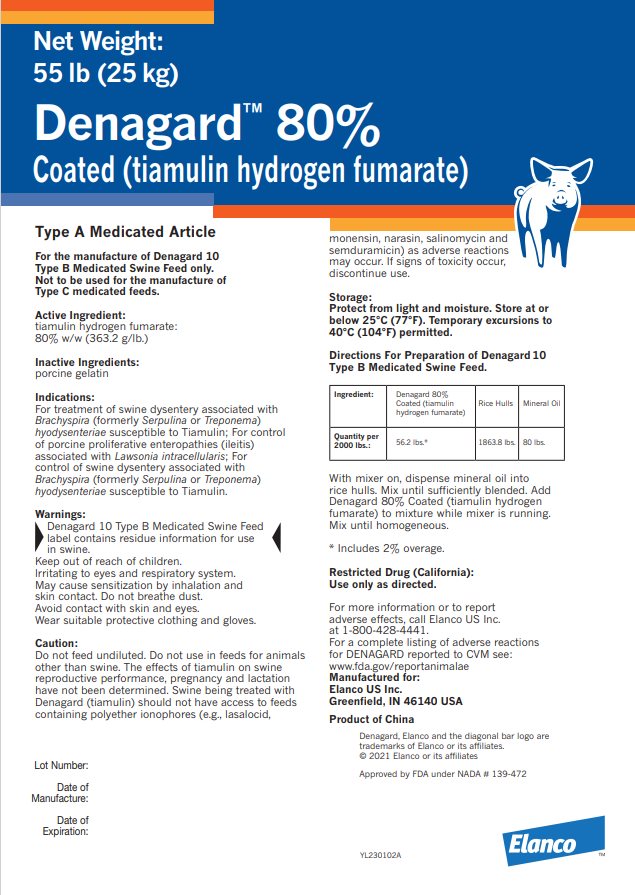 DRUG LABEL: Denagard 80 coated Type A Medicated Article
NDC: 58198-9413 | Form: POWDER
Manufacturer: Elanco US Inc.
Category: animal | Type: OTC ANIMAL DRUG LABEL
Date: 20251121

ACTIVE INGREDIENTS: Tiamulin Fumarate 22 g/1 kg

Net Weight:
55 lb (25 kg)
Denagard™ 80%

Coated (tiamulin hydrogen fumarate)

Type A Medicated Article

For the manufacture of Denagard 10
Type B Medicated Swine Feed only.
Not to be used for the manufacture of
Type C medicated feeds.

Active Ingredient:

tiamulin hydrogen fumarate:
80% w/w (363.2 g/lb.)

Inactive Ingredients:

porcine gelatin

Indications:

For treatment of swine dysentery associated with Brachyspira (formerly Serpulina or Treponema) hyodysenteriae susceptible to Tiamulin; For control of porcine proliferative enteropathies (ileitis) associated with Lawsonia intracellularis; For control of swine dysentery associated with Brachyspira (formerly Serpulina or Treponema) hyodysenteriae susceptible to Tiamulin.

Warnings:

Denagard 10 Type B Medicated Swine Feed label contains residue information for use in swine.

Keep out of reach of children.

lrritating to eyes and respiratory system.

May cause sensitization by inhalation and skin contact. Do not breathe dust.

Avoid contact with skin and eyes.

Wear suitable protective clothing and gloves.

Caution:

Do not feed undiluted. Do not use in feeds for animals other than swine. The effects of tiamulin on swine reproductive performance, pregnancy and lactation have not been determined. Swine being treated with Denagard (tiamulin) should not have access to feeds containing polyether ionophores (e.g., lasalocid, monensin, narasin, salinomycin and semduramicin) as adverse reactions may occur. If signs of toxicity occur, discontinue use.

Storage:

Protect from light and moisture. Store at or below 25°C (77°F). Temporary excursions to 40°C (104°F) permitted.

Directions For Preparation of Denagard 10 Type B Medicated Swine Feed.

Ingredient: | Denagard 80% Coated (tiamulin hydrogen fumarate) | Rice Hulls | Mineral Oil
Quantity per 2000 lbs.: | 56.2 lbs.* | 1863.8 lbs. | 80 lbs.

With mixer on, dispense mineral oil into rice hulls. Mix until sufficiently blended. Add Denagard 80% Coated (tiamulin hydrogen fumarate) to mixture while mixer is running. Mix until homogeneous.

* Includes 2% overage.

Restricted Drug (California):
Use only as directed.

For more information or to report adverse effects, call Elanco US Inc. at 1-800-428-4441.

For a complete listing of adverse reactions for DENAGARD reported to CVM see:
www.fda.gov/reportanimalae

Manufactured for:
Elanco US Inc.
Greenfield, IN 46140 USA
Product of Italy
Product of China

Lot Number:

Date of
Manufacture:

Date of
Expiration:

Denagard, Elanco and the diagonal bar logo are trademarks of Elanco or its affiliates.
© 2023 Elanco or its affiliates
© 2021 Elanco or its affiliates

Approved by FDA under NADA # 139-472

YL240600X
YL230102A

Elanco™

Principal Display Panel - 22 g in 1 kg Bag Label

Net Weight:
55 lb (25 kg)
Denagard™ 80%
Coated (tiamulin hydrogen fumarate)
Type A Medicated Article
Approved by FDA under NADA # 139-472

Net Weight:
55 lb (25 kg)
Denagard™ 80%
Coated (tiamulin hydrogen fumarate)
Type A Medicated Article
Approved by FDA under NADA # 139-472